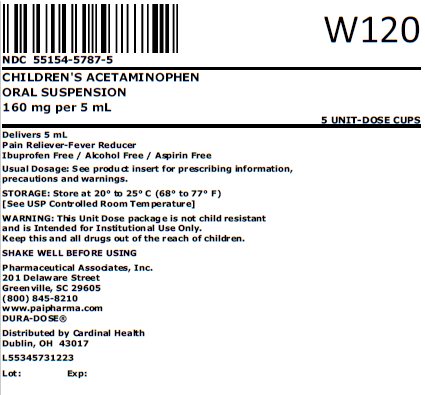 DRUG LABEL: Childrens Acetaminophen
NDC: 55154-5787 | Form: SUSPENSION
Manufacturer: Cardinal Health 107, LLC
Category: otc | Type: HUMAN OTC DRUG LABEL
Date: 20250923

ACTIVE INGREDIENTS: ACETAMINOPHEN 160 mg/5 mL
INACTIVE INGREDIENTS: ACESULFAME POTASSIUM; BUTYLPARABEN; ANHYDROUS CITRIC ACID; FD&C RED NO. 40; GLYCERIN; HIGH FRUCTOSE CORN SYRUP; POLYSORBATE 80; PROPYLENE GLYCOL; WATER; SODIUM BENZOATE; SORBITOL SOLUTION; MAGNESIUM ALUMINUM SILICATE; XANTHAN GUM

Children's Acetaminophen Oral Suspension
Ibuprofen Free/Alcohol Free/Aspirin Free

Active ingredient (in each 5 mL)

Acetaminophen 160 mg

Purpose

Pain reliever/fever reducer

Uses

temporarily:

- reduces fever
- relieves minor aches and pain due to:
  - the common cold
  - flu
  - headache
  - sore throat
  - toothache

Warnings

Liver warning: This product contains contains acetaminophen. Severe liver damage may occur if your child takes:
• more than 5 doses in 24 hours, which is the maximum daily amount
• with other drugs containing acetaminophen

Allergy alert: acetaminophen may cause severe skin reactions.

Symptoms may include:
• skin reddening
• blisters
• rash

If a skin reaction occurs, stop use and seek medical help right away.

Sore throat warning: if sore throat is severe, persists for more than 2 days, is accompanied or followed by fever, headache, rash, nausea, or vomiting, consult a doctor promptly

Do not use
• with any other drug containing acetaminophen (prescription or nonprescription). If you are not sure whether a drug contains acetaminophen, ask a doctor or pharmacist.
• if your child is allergic to acetaminophen or any of the inactive ingredients in this product.

Ask a doctor before use if your child has liver disease.

Ask a doctor or pharmacist before use if your child is taking the blood thinning drug warfarin.

When using this product, do not exceed the recommended dose (see overdose warning)

Stop use and ask a doctor if:
• pain gets worse or lasts more than 5 days
• fever gets worse or lasts more than 3 days
• new symptoms occur
• redness or swelling is present

These could be signs of a serious condition.

Keep out of the reach of children.

Overdose warning: In case of overdose, get medical help or contact a Poison Control Center right away. (1-800-222-1222). Quick medical attention is critical for adults as well as children even if you do not notice any sign or symptoms

Directions

- this product does not contain directions or complete warnings for adult use
- do not take more than directed (see overdose warning)
- shake well before using
- mL = milliliter
- find the right dose on chart below. If possible, use weight to dose; otherwise, use age
- repeat dose every 4 hours while symptoms last
- do not give more than 5 times in 24 hours

Weight (lbs) | Age (yr) | Dose (mL) [or as directed by a doctor]
Under 24 | Under 2 | Ask a doctor
24-35 | 2-3 years | 5 mL
36-47 | 4-5 years | 7.5 mL
48-59 | 6-8 years | 10 mL
60-71 | 9-10 years | 12.5 mL
72-95 | 11 years | 15 mL

Other information

- each 5 mL contains: sodium 2 mg
- Store at 20° to 25°C (68° to 77°F). [See USP Controlled Room Temperature]
- protect from freezing
- a red, berry flavored suspension supplied in the following oral dosage form

Overbagged with 5 x 5 mL unit dose cup in each bag, NDC 55154-5787-5

WARNING: This Unit Dose package is not child resistant and is Intended for Institutional Use Only. Keep this and all drugs out of the reach of children.

Inactive ingredients

Acesulfame K, butylparaben, citric acid, FD&C Red No. 40, flavoring, glycerin, high fructose corn syrup, polysorbate 80, propylene glycol, purified water, sodium benzoate, sorbitol solution, veegum and xanthan gum.

Questions or comments?

Call 1-800-845-8210.

MANUFACTURED BY

Pharmaceutical Associates, Inc.

Greenville, SC 29605

www.paipharma.com

Distributed By:

Cardinal Health

Dublin, OH 43017

L55345731223

R09/20

Principal Display Panel

NDC 55154-5787-5

CHILDREN’S ACETAMINOPHEN

ORAL SUSPENSION

160 mg per 5 mL

5 UNIT-DOSE CUPS